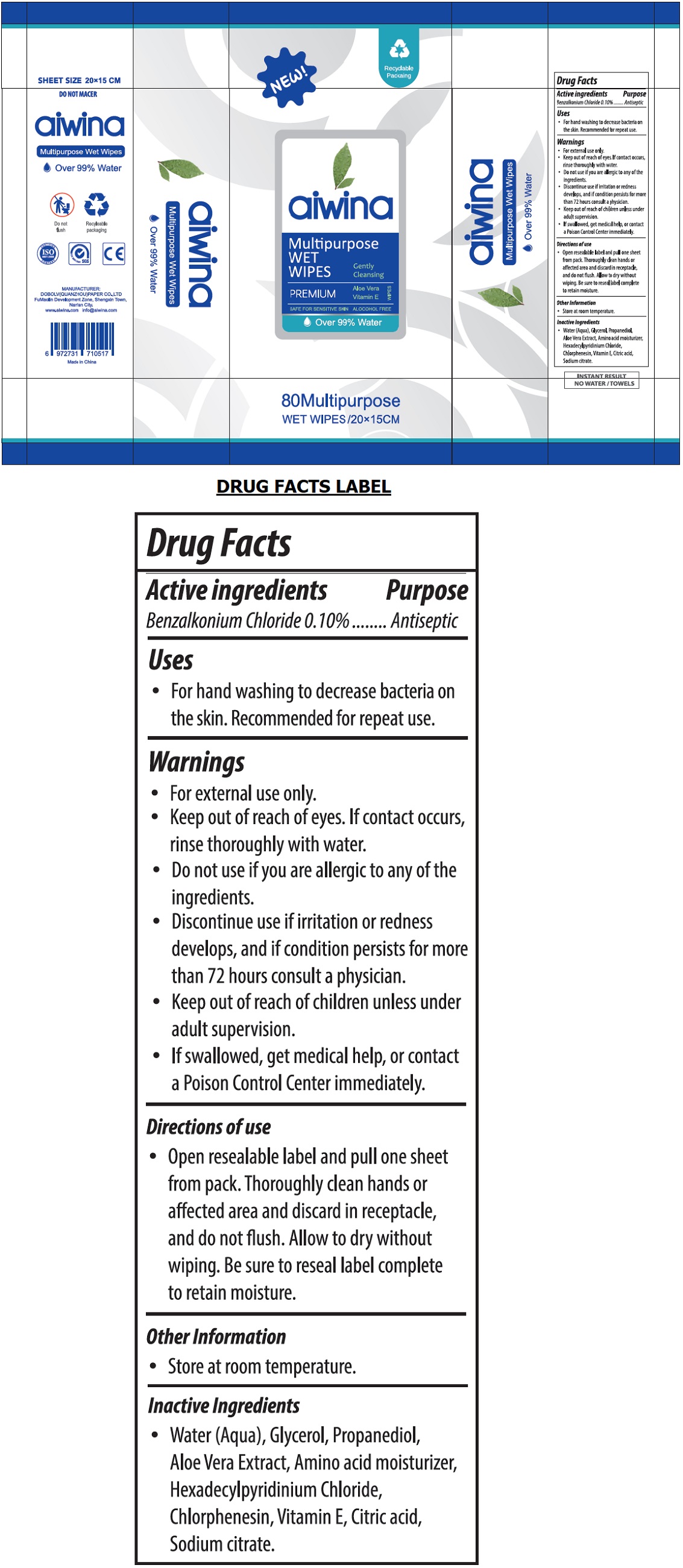 DRUG LABEL: aiwina WET WIPES
NDC: 79891-001 | Form: CLOTH
Manufacturer: DOBOLV (QUANZHOU) PAPER CO., LTD
Category: otc | Type: HUMAN OTC DRUG LABEL
Date: 20200807

ACTIVE INGREDIENTS: BENZALKONIUM CHLORIDE 0.1 g/100 mL
INACTIVE INGREDIENTS: WATER; GLYCERIN; PROPANEDIOL; ALOE VERA LEAF; BETAINE; CETYLPYRIDINIUM CHLORIDE; CHLORPHENESIN; .ALPHA.-TOCOPHEROL; CITRIC ACID MONOHYDRATE; SODIUM CITRATE, UNSPECIFIED FORM

aiwina Multipurpose WET WIPES

Active ingredients

Benzalkonium Chloride 0.10%

Purpose

Antiseptic

Uses

• For hand washing to decrease bacteria on the skin. Recommended for repeated use.

Warnings

• For external use only.

• Keep out of reach of eyes. If contact occurs, rinse thoroughly with water.

• Do not use if you are allergic to any one of the ingredients.

• Discontinue use if irritation or redness develops, and if condition persists for more than 72 hours consult a physician

• Keep out of reach of children unless under adult supervision.

• If swallowed, get medical help, or contact a Poison Control Center immediately.

Directions of use

• Open resealable label and pull one sheet from pack. Thoroughly clean hands or affected area and discard in receptacle, and do not flush. Allow to dry without wiping. Be sure to reseal label complete to retain moisture.

Other Information

• Store at room temperature.

Inactive Ingredients

• Water (Aqua), Glycerol, Propanediol, Aloe Vera Extract, Amino acid moisturizer, Hexadecylpyridinium Chloride, Chlorphenesin, Vitamin E, Citric acid, Sodium citrate.

NEW!

Recyclable Packaging

Gently Cleansing

PREMIUM Aloe Vera Vitamin E WIPES

SAFE FOR SENSITIVE SKIN ALCOHOL FREE

Over 99% Water

SHEET SIZE 20X15 CM

DO NOT MACER

Do not flush

CERTIFIED ISO 9001:2008 COMPANY

SYSTEM CERTIFICATION ISO 9001:2008 SGS

MANUFACTURER:

DOBOLV (QUANZHOU)PAPER CO., LTD

FuMaolin Development Zone, Shengxin Town,

Nan'an City.

www.aiwina.com

info@aiwina.com

Made in China

INSTANT RESULT

NO WATER/ TOWELS